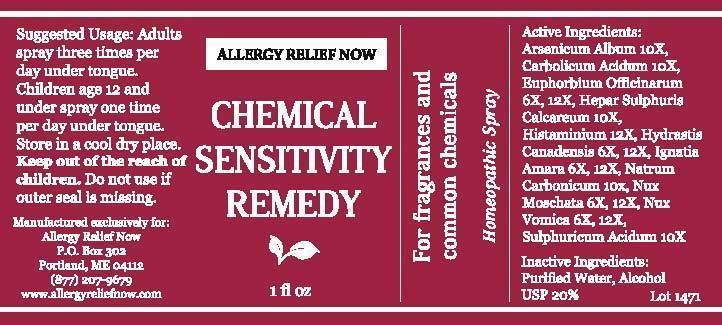 DRUG LABEL: Allergy Relief Now Chemical Sensitivity Remedy
NDC: 61727-050 | Form: SPRAY
Manufacturer: Homeocare Laboratories
Category: homeopathic | Type: HUMAN OTC DRUG LABEL
Date: 20140324

ACTIVE INGREDIENTS: ARSENIC TRIOXIDE 10 [hp_X]/1 [hp_X]; PHENOL 10 [hp_X]/1 [hp_X]; EUPHORBIA RESINIFERA RESIN 6 [hp_X]/1 [hp_X]; CALCIUM SULFIDE 10 [hp_X]/1 [hp_X]; HISTAMINE 12 [hp_X]/1 [hp_X]; GOLDENSEAL 6 [hp_X]/1 [hp_X]; STRYCHNOS IGNATII SEED 6 [hp_X]/1 [hp_X]; SODIUM CARBONATE 10 [hp_X]/1 [hp_X]; NUTMEG 6 [hp_X]/1 [hp_X]; STRYCHNOS NUX-VOMICA SEED 6 [hp_X]/1 [hp_X]; SULFURIC ACID 10 [hp_X]/1 [hp_X]
INACTIVE INGREDIENTS: WATER; ALCOHOL

Active Ingredients:

Arsenicum Album 10X, Carbolicum Acidum 10X, Euphorbium Officinarum 6X, 12X, Hepar Sulphuris Calcareum 10X, Histaminium 12X, Hydrastis Canadensis 6X, 12X, Ignatia Amara 6X, 12X, Natrum Carbonicum 10X, Nux Moschata 6X, 12X, Nux Vomica 6X, 12X, Sulphuricum Acidum 10X

Suggested Use:

Adults spray three times per day under tongue. Children age 12 and under spray one time per day under tongue. Store in a cool dry place.

Inactive Ingredients:

Purified Water, Alcohol USP 20%

INDICATIONS AND USAGE

For frangrances and common chemicals Homeopathic Spray

Keep out of the reach of children

Do not use if outer seal is missing

Allergy Relief Now Chemical Sensitivity Remedy 1 fl oz

Concordia_LabelFinal-ChemSensitivity-1471.jpg